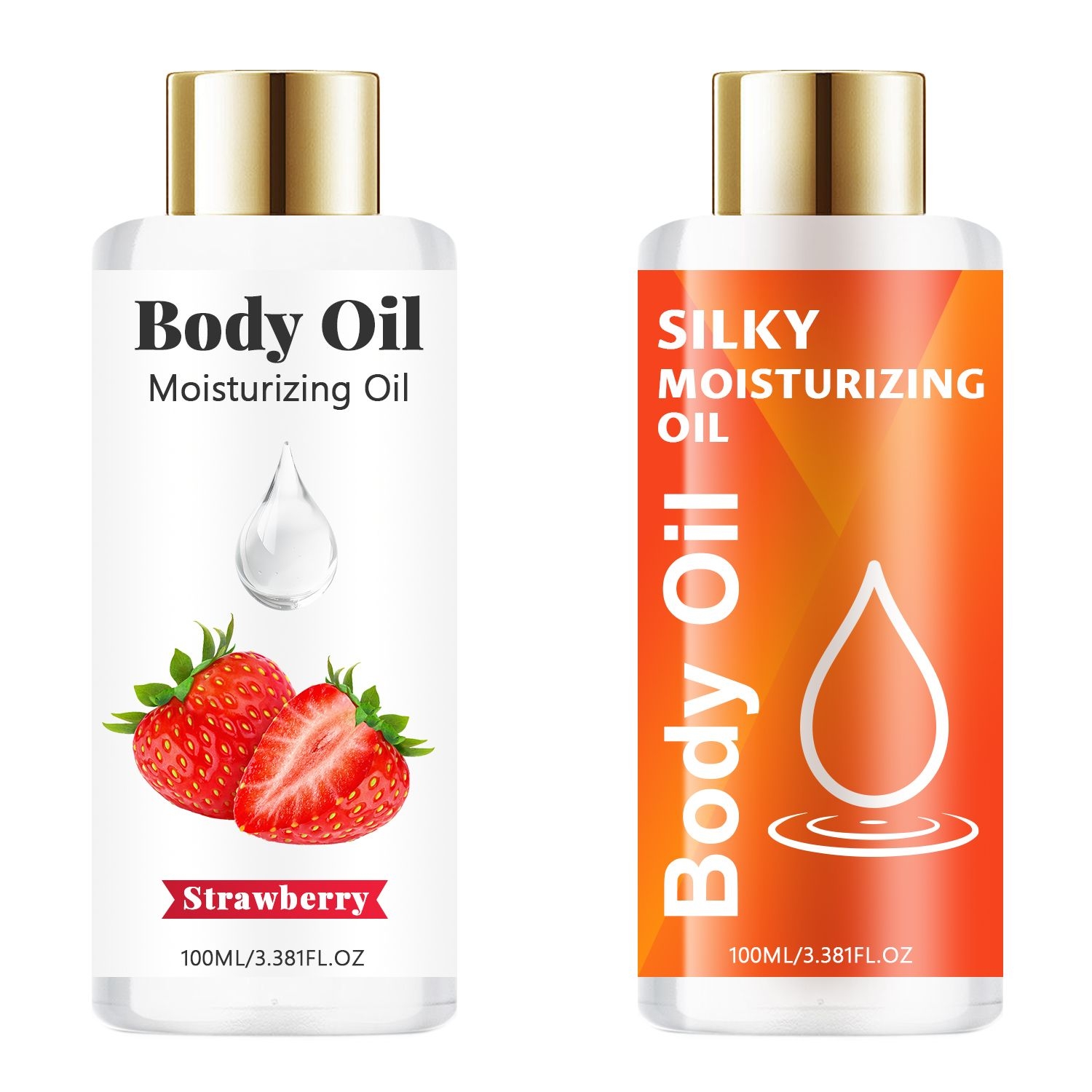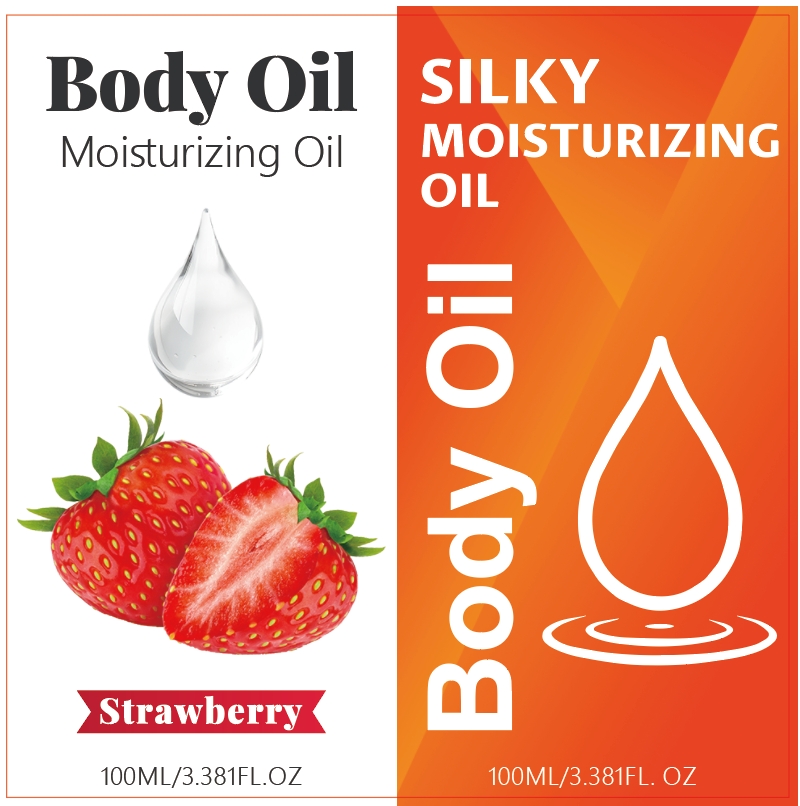 DRUG LABEL: Body Oil
NDC: 84025-217 | Form: OIL
Manufacturer: Guangzhou Yanxi Biotechnology Co., Ltd
Category: otc | Type: HUMAN OTC DRUG LABEL
Date: 20241016

ACTIVE INGREDIENTS: HYALURONIC ACID 3 mg/100 mL; GLYCERIN 5 mg/100 mL
INACTIVE INGREDIENTS: WATER

DOSAGE AND ADMINISTRATION

Apply morning and night all over your body, Follow with moisturizer.

WARNINGS

keep out of children

INACTIVE INGREDIENT

Aqua

INDICATIONS AND USAGE

Lightweight body oil for dry skin pampers your skin as a sheer moisturizer that instantly vanishes and absorbs quickly into skin, providing essential hydration while locking in moisture without leaving a greasy feel

keep out of children

PURPOSE

Lightweight body oil for soft and silky skin